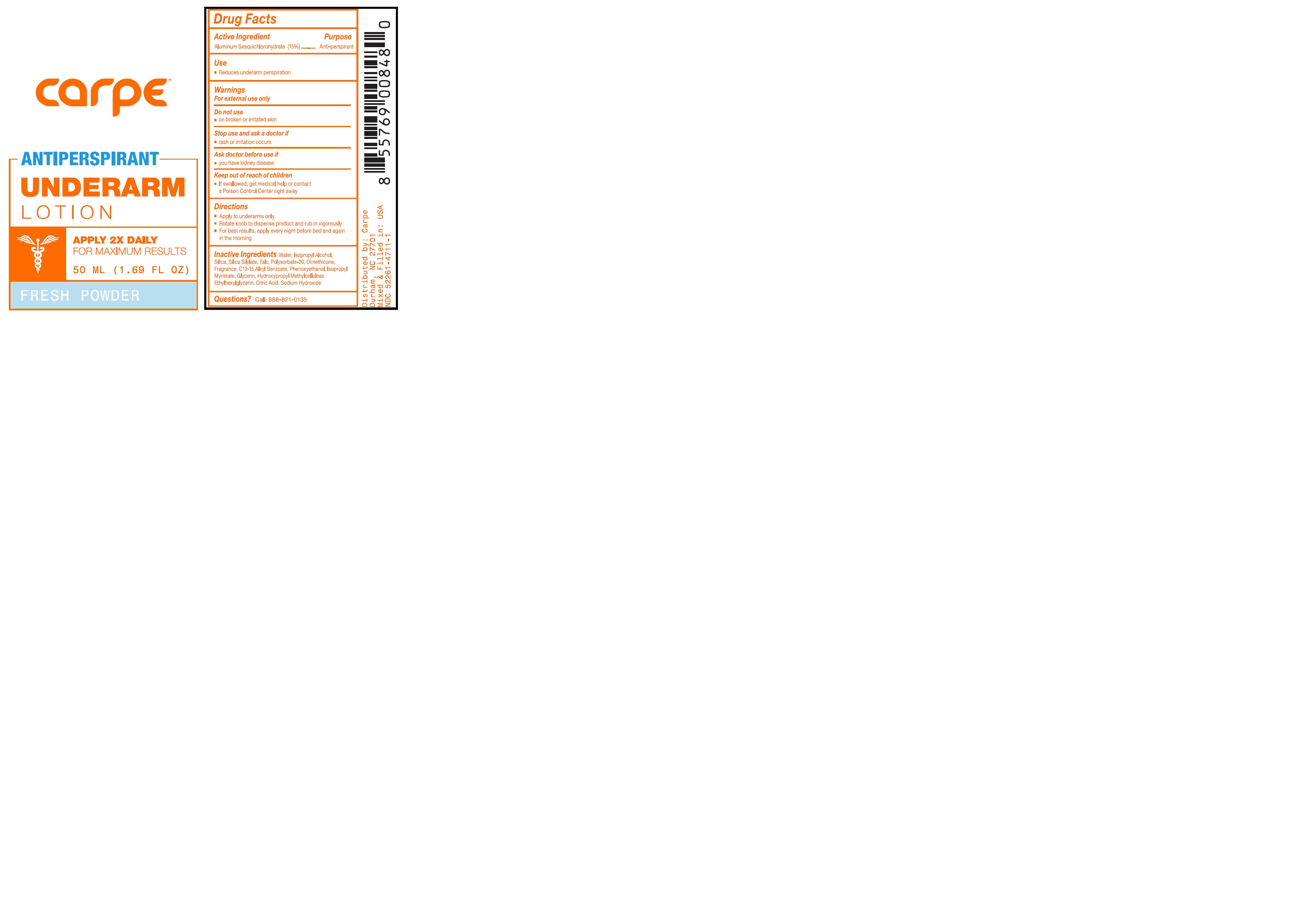 DRUG LABEL: Carpe Antiperspirant Underarm Fresh Powder Scent
NDC: 52261-4711 | Form: Lotion
Manufacturer: Cosco International, Inc.
Category: otc | Type: HUMAN OTC DRUG LABEL
Date: 20220721

ACTIVE INGREDIENTS: Aluminum Sesquichlorohydrate 0.15 kg/1 kg
INACTIVE INGREDIENTS: water; isopropyl alcohol; SILICON DIOXIDE; HEXAMETHYLDISILAZANE; talc; polysorbate 20; dimethicone 350; ALKYL (C12-15) BENZOATE; phenoxyethanol; ISOPROPYL MYRISTATE; glycerin; HYPROMELLOSE 2208 (100000 MPA.S); sodium hydroxide; citric acid monohydrate; ethylhexylglycerin

Drug Facts

Active Ingredient Purpose
Aluminum Sesquicholorhydrate 15% .......................Anti-perspirant

PURPOSE

Anti-perspirant

Use

- Reduces underarm perspiration

Warnings

For external use only

Do not use

- on broken or irritated skin

Stop use and ask a doctor if

- rash or irritation occurs

Ask doctor before use if

- you have kidney disease

Keep out of reach of children

- If swallowed, get medical help or contact a Poison Control Center right away

Directions

- Apply to underarms only
- Rotate knob to dispense product and rub in vigorously
- For best results, apply every night before bed and again in the morning

Inactive ingredients

Water, Isopropyl Alcohol, Silica, Silica Silylate, Talc, Polysorbate-20, Dimethicone, Fragrance, C12-15 Alkyl Benzoate, Phenoxyethanol, Isopropyl Myristate, Glycerin, Hydroxypropyl Methylcellulose, Ethylhexylglycerin, Citric Acid, Sodium Hydroxide

Questions?

Call 888-621-0135